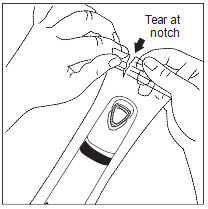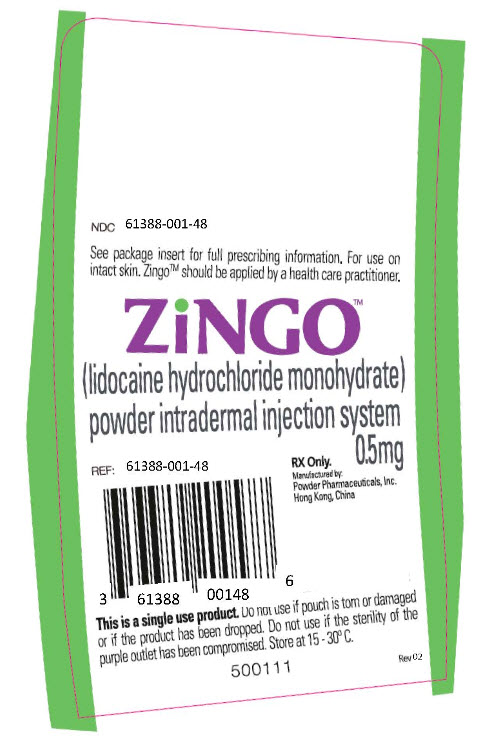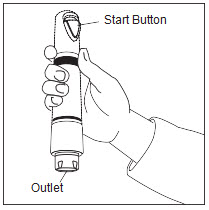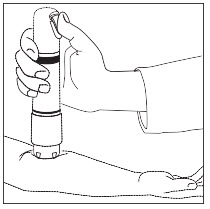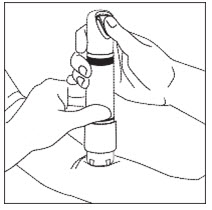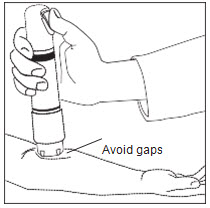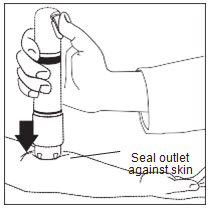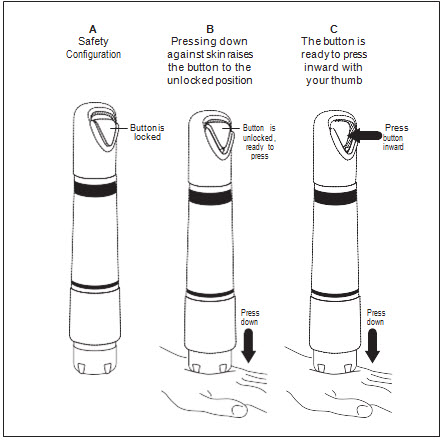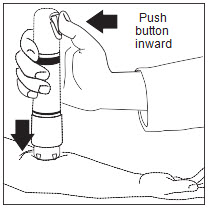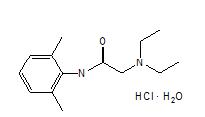 DRUG LABEL: Zingo
NDC: 61388-001 | Form: POWDER
Manufacturer: Powder Pharmaceuticals Inc.
Category: prescription | Type: HUMAN PRESCRIPTION DRUG LABEL
Date: 20131101

ACTIVE INGREDIENTS: LIDOCAINE HYDROCHLORIDE 0.5 mg/1 1

HIGHLIGHTS OF PRESCRIBING INFORMATION

These highlights do not include all the information needed to use Zingo™ safely and effectively. See full prescribing information for Zingo™.
Zingo™ (lidocaine hydrochloride monohydrate) powder intradermal injection system
Initial U.S. Approval: 1948

1 INDICATIONS AND USAGE

- Zingo™ is an amide local anesthetic indicated for use on intact skin to provide local analgesia prior to venipuncture or peripheral intravenous cannulation in children 3–18 years of age. (1)
- Zingo™ is indicated for use on intact skin to provide topical local analgesia prior to venipuncture in adults. (1)

Important Limitations:

- For use on intact skin only (1, 2)
- For external use only (5)

2 DOSAGE AND ADMINISTRATION

- Apply one Zingo™ (0.5 mg lidocaine hydrochloride monohydrate) to the site planned for venipuncture or intravenous cannulation, one to three minutes prior to needle insertion. (2.1)
- Perform the procedure within 10 minutes after Zingo™ administration. (2)
- Use Zingo™ only on intact skin. (2)

3 DOSAGE FORMS AND STRENGTHS

Zingo™ is a sterile, single-use, powder intradermal injection system containing 0.5 mg lidocaine hydrochloride monohydrate. (3)

Zingo™ utilizes a helium-powered delivery system. (11)

4 CONTRAINDICATIONS

Zingo™ is contraindicated in patients with a known history of sensitivity to local anesthetics of the amide type. (4)

5 WARNINGS AND PRECAUTIONS

- Use on intact skin only (2.1, 5)
- Avoid contact with the eye (2.1, 5)
- Do not use if device is dropped or the pouch is damaged or torn (2.1)
- Patients with bleeding tendencies or platelet disorders could have a higher risk of superﬁcial dermal bleeding (5)

6 ADVERSE REACTIONS

The most common adverse reactions (>5%) are skin reactions at the site of administration: erythema, petechiae, edema, and pruritus (6.1)

To report SUSPECTED ADVERSE REACTIONS, contact Marathon Pharmaceuticals, LLC, at 1-866-562-4620 or FDA at 1-800-FDA-1088 or www.fda.gov/medwatch.

FULL PRESCRIBING INFORMATION

1 INDICATIONS AND USAGE

Zingo™ is indicated for use on intact skin to provide topical local analgesia prior to venipuncture or peripheral intravenous cannulation, in children 3–18 years of age.

Zingo™ is indicated for use on intact skin to provide topical local analgesia prior to venipuncture in adults.

2 DOSAGE AND ADMINISTRATION

Apply one Zingo™ (0.5 mg lidocaine hydrochloride monohydrate) to the site planned for venipuncture or intravenous cannulation, one to three minutes prior to needle insertion.

Perform the procedure within 10 minutes after Zingo™ administration. Use Zingo™ only on intact skin.

Application of one additional Zingo™ at a new location is acceptable after a failed attempt at venous access. Multiple administrations of Zingo™ at the same location are not recommended.

When Zingo™ is used concomitantly with other products containing local anesthetic agents, the amount absorbed from all sources should be considered, as local anesthetics are thought to have at least additive toxicities.

2.1 Instructions for Use

Prepare the Treatment Site and Device:

Examine the treatment site to ensure that the skin is intact. Clean the site, according to standard practice.

Visually inspect the pouch. Do not use if the pouch has been torn, or damaged or if the device has been dropped.

Tear open the pouch using the notch provided (Figure 1a). Remove ZingoTM from the pouch, being careful not to touch the purple outlet (open end) to avoid contamination (Figure 1b).

Figure 1a

Figure 1b

Position Zingo™: Grip Zingo™ and place on the application site, with one hand, as illustrated in Figure 2, or with both hands, as shown in Figure 3.

Figure 2

Figure 3

Ensure that the patient’s treatment site is supported to prevent movement. Seal the purple Zingo™ outlet against the patient’s skin. Hold the device perpendicular to the skin, making sure that your thumb can reach the green start button.

Avoid gaps between the skin and the Zingo™ outlet, like the one illustrated in Figure 4, as gaps will impede drug delivery.

Figure 4

Release the Safety Interlock: Apply adequate downward pressure to release the safety interlock, while maintaining the seal between Zingo™ and the skin.

Zingo™ is ready for administration when the green start button has moved into the upward position, as illustrated in Figure 5a.

Figure 5a

Zingo™ cannot be actuated without releasing the internal safety interlock, as illustrated in Figure 5b.

Figure 5b

Administer Zingo™: While maintaining downward pressure, administer the dose by pressing the green start button, as illustrated in Figure 6. Do not move Zingo™ during administration. Actuation is accompanied by a “popping” sound, indicating that the dose has been discharged.

Figure 6

Remove Zingo™: Remove Zingo™ from the application site and dispose.

Begin Procedure: Start the venipuncture or intravenous cannulation procedure 1–3 minutes after Zingo™ administration.

3 DOSAGE FORMS AND STRENGTHS

Zingo™ (lidocaine hydrochloride monohydrate) powder intradermal injection system contains 0.5 mg of sterile lidocaine hydrochloride monohydrate.

4 CONTRAINDICATIONS

Zingo™ is contraindicated in patients with a known history of sensitivity to local anesthetics of the amide type.

5 WARNINGS AND PRECAUTIONS

Do not use around the eyes.

Do not use Zingo™ on body oriﬁces, mucous membranes, or on areas with a compromised skin barrier. Only use Zingo™ on skin locations where an adequate seal can be maintained.

Patients with severe hepatic disease or pseudocholinesterase deﬁciency, because of their inability to metabolize local anesthetics normally, are at a greater risk of developing toxic plasma concentrations of lidocaine.

Patients with bleeding tendencies or platelet disorders could have a higher risk of superﬁcial dermal bleeding.

6 ADVERSE REACTIONS

6.1 Clinical Trials Experience

Because clinical trials are conducted under widely varying conditions, adverse reaction rates observed in the clinical trials of a drug cannot be directly compared to rates in the clinical trials of another drug and may not reﬂect the rates observed in clinical practice.

The safety of Zingo™ has been evaluated in 10 clinical trials, ﬁve in adults and ﬁve in pediatric patients.

The ﬁve adult clinical trials consisted of a randomized, double-blind, parallel-arm, sham-placebo controlled Phase 3 trial that enrolled 693 patients, two randomized, double-blind, crossover design, sham-placebo controlled Phase 1 trials that enrolled 455 patients, and two open-label studies that enrolled 44 patients. A total of 742 adults received an active treatment with an active treatment that delivered a 0.5 mg dose of lidocaine, while 775 received placebo.

The ﬁve pediatric clinical trials consisted of ﬁve randomized, double-blind, parallel-arm, sham- placebo controlled trials in which 1761 patients, ages 3 to 18, received either Zingo™ or a sham placebo device. A total of 906 pediatric patients received active treatment, while 855 received placebo.

Application Site Reaction

The application site was speciﬁcally assessed for four categories of skin site reaction (erythema, edema, pruritus, and petechiae).

In adults, erythema occurred in 67.3% of Zingo™-treated patients, and in 25.0% of placebo- treated patients. Petechiae occurred in 46.4% of Zingo™-treated patients, and in 7.0% of placebo-treated patients. Edema occurred in 4.3% of Zingo™-treated patients, and in 0.8% of placebo-treated patients. Pruritus occurred in 9.4% of Zingo™-treated patients and in 6.2% of placebo-treated patients.

In pediatric patients, erythema occurred in 53% of Zingo-treated patients, and in 27% of placebo-treated patients. Petechiae occurred in 44% of Zingo-treated patients, and in 5% of placebo-treated patients. Edema occurred in 8% of Zingo-treated patients, and in 3% of placebo-treated patients. Pruritus occurred in 1% of patients in both treatment groups.

Adverse Reactions

Amongst the 742 adult patients receiving active treatment and 775 adult patients receiving sham placebo treatment in the 5 adult studies, the percentage of adult patients with any adverse reactions was 3.9% in the active-treated patients and 4.9% in the sham placebo treated patients.

Most adverse reactions were application-site related (i.e., hypoaesthesia (0% active, 0.5% sham placebo), burning (0.54% active, 0.4% sham placebo), and venipuncture site hemorrhage (0.4% active, 1.7% sham placebo)).

The most common systemic adverse reaction was dizziness, which occurred in 0.9% of active- treated adult patients and in 0.7% of sham placebo treated adult patients. No other systemic adverse events occurred in more than two patients in either treatment group.

Amongst the 906 pediatric patients receiving active treatment and 855 pediatric patients receiving sham placebo treatment, the percentage of pediatric patients with any adverse reactions was approximately 9% in each treatment group.

Most adverse reactions were application-site related (i.e., bruising, burning, pain, contusion, hemorrhage), occurring in 4% of pediatric patients in each treatment group.

The most common systemic adverse reactions were nausea (2%) and vomiting (1%).

8 USE IN SPECIFIC POPULATIONS

8.1 Pregnancy

Zingo™ was not formally evaluated for effects on reproduction. Signiﬁcant systemic exposure to lidocaine is not expected under recommended conditions of use of Zingo™ as lidocaine levels were below the limit of detection in human studies. Lidocaine has been previously tested for reproductive toxicity in animal studies, however. The following ratios are based on the assumption that the applied dose is completely absorbed through the skin.

Teratogenic Effects

Pregnancy Category B. Lidocaine was not teratogenic in rats given subcutaneous doses up to 60 mg/kg [360 mg/m^2 or 1200-fold the single dermal administration (SDA) of 0.5 mg lidocaine in a 60 kg individual (0.3 mg/m^2)] or in rabbits up to 15 mg/kg (180 mg/m2 or 600-fold the SDA).

There are, however, no adequate and well-controlled studies in pregnant women. Because animal reproduction studies are not always predictive of human response, Zingo™ should be used during pregnancy only if clearly needed.

Nonteratogenic Effects

Lidocaine, containing 1:100,000 epinephrine, at a dose of 6 mg/kg (36 mg/m or 120-fold the SDA) injected into the masseter muscle of the jaw or into the gum of the lower jaw of Long- Evans hooded pregnant rats on gestation day 11 led to developmental delays in neonatal behavior among offspring. Developmental delays were observed for negative geotaxis, static righting reﬂex, visual discrimination response, sensitivity and response to thermal and electrical shock stimuli, and water maze acquisition. The developmental delays of the neonatal animals were transient with responses becoming comparable to untreated animals later in life. The clinical relevance of the animal data is uncertain. No adequate and well–controlled studies have been conducted in pregnant women. Because animal studies are not always predictive of human response, Zingo™ should be used during pregnancy only if the potential beneﬁt justiﬁes risk to the fetus.

8.2 Labor and Delivery

Lidocaine is not contraindicated in labor and delivery. In humans, the use of lidocaine for labor conduction analgesia has not been associated with an increased incidence of adverse fetal effects either during delivery or during the neonatal period. Should Zingo™ be used concomitantly with other products containing lidocaine, total doses contributed by all formulations must be considered.

8.3 Nursing Mothers

Lidocaine is excreted into human milk; therefore, caution should be exercised when Zingo™ is administered to a nursing mother. Because no plasma concentrations of lidocaine are detected after topical administration of Zingo™ in recommended doses, the small amount of lidocaine that would be ingested orally by a suckling infant is unlikely to cause adverse effects.

8.4 Pediatric Use

Safety and effectiveness in pediatric patients below the age of 3 years have not been established.

8.5 Geriatric Use

Of the 693 patients evaluated in a Phase 3 randomized, double blind, sham-placebo-controlled trial in adults, 17% were of 65 and over. The safety and effectiveness of Zingo™ in geriatric patients were similar to that of Zingo™ in adults under 65 years of age.

9 DRUG ABUSE AND DEPENDENCE

Zingo™ is not known to possess drug abuse or dependence potential.

10 OVERDOSAGE

In adults following a single administration of Zingo™ the plasma levels of lidocaine were below the limit of detection (5 ng/mL). Signs of central nervous system (CNS) toxicity may start at plasma concentrations of lidocaine as low as 1000 ng/mL, and the risk of seizures generally increases with increasing plasma levels. Very high levels of lidocaine can cause respiratory arrest, coma, decreases in cardiac output, total peripheral resistance, and mean arterial pressure, ventricular arrhythmias, and cardiac arrest. The toxicity of coadministered local anesthetics is thought to be at least additive. In the absence of massive topical overdose or oral ingestion, other etiologies for the clinical effects or overdosage from other sources of lidocaine or other local anesthetics should be considered. The management of overdosage includes close monitoring, supportive care, and symptomatic treatment. Dialysis is of negligible value in the treatment of acute overdosage of lidocaine.

11 DESCRIPTION

Zingo™ (lidocaine hydrochloride monohydrate) powder intradermal injection system contains 0.5 mg of sterile lidocaine hydrochloride monohydrate.

The chemical name is 2-diethylamino-2',6'-acetoxylidide, monohydrochloride, monohydrate. The molecular formula is C14H22N2O · HCl · H2O with a molecular weight of 288.8 Da. Lidocaine hydrochloride monohydrate, a local anesthetic of the amide class, has the following structural formula:

Lidocaine hydrochloride monohydrate is freely soluble in water, soluble in alcohol and chloroform, insoluble in ether, and melts at around 74–79°C.

Zingo™ is a ready-to-use, sterile, single-use, disposable, needle-free delivery system. Zingo™ consists of the following components: a drug reservoir cassette ﬁlled with 0.5 mg lidocaine hydrochloride monohydrate as a powder with a nominal particle size of 40 μm, a pressurized helium gas cylinder, and a safety interlock. The safety interlock prevents inadvertent actuation of the device. Once Zingo™ is pressed against the skin, the interlock is released, allowing the button to be depressed to actuate the device. A sound similar to that of a popping balloon is emitted at the time Zingo™ is actuated.

12 CLINICAL PHARMACOLOGY

12.1 Mechanism of Action

Zingo™ delivers lidocaine hydrochloride monohydrate into the dermis. Lidocaine is an amide- type local anesthetic agent that blocks sodium ion channels required for the initiation and conduction of neuronal impulses, resulting in local anesthesia.

12.2 Pharmacodynamics

Zingo™ provides local dermal analgesia within 1–3 minutes of application. Analgesia diminishes within 10 minutes of treatment.

12.3 Pharmacokinetics

Absorption

A single dose of Zingo™ in adults did not produce detectable plasma concentrations of lidocaine (limit of quantitation 5 ng/mL) in any subject tested (n = 38).

Application of Zingo™ to broken or inﬂamed skin, or multiple Zingo™ applications, could result in systemic plasma levels of lidocaine that could produce systemic toxicity.

Distribution

When lidocaine is administered intravenously to healthy volunteers, the steady-state volume of distribution is approximately 0.8 to 1.3 L/kg. At much higher plasma concentrations (1 to 4 mcg/ mL of free base) than those found following application of Zingo™, the plasma protein binding of lidocaine is concentration dependent. Lidocaine crosses the placental and blood brain barriers, presumably by passive diffusion. CNS toxicity may typically be observed around 5000 ng/mL of lidocaine; however a small number of patients reportedly may show signs of toxicity at approximately 1000 ng/mL.

Metabolism

It is not known if lidocaine is metabolized in the skin. Lidocaine is metabolized rapidly by the liver to a number of metabolites including monoethylglycinexylidide (MEGX) and glycinexylidide (GX), both of which have pharmacologic activity similar to, but less potent than that of lidocaine. The major metabolic pathway of lidocaine, sequential N-deethylation to monoethylglycinexylidide (MEGX) and glycinexylidide (GX), is primarily mediated by CYP1A2 with a minor role of CYP3A4. The metabolite, 2,6-xylidine, has unknown pharmacologic activity. Following intravenous administration of lidocaine, MEGX and GX concentrations in serum range from 11% to 36% and from 5% to 11% of lidocaine concentrations, respectively. Serum concentrations of MEGX are about one-third the serum lidocaine concentrations.

Elimination

The half-life of lidocaine elimination from the plasma following intravenous administration is approximately 1.8 hours. Lidocaine and its metabolites are excreted by the kidneys. More than 98% of an absorbed dose of lidocaine can be recovered in the urine as metabolites or parent drug. Less than 10% of lidocaine is excreted unchanged in adults, and approximately 20% is excreted unchanged in neonates. The systemic clearance is approximately 8–10 mL/min/kg. During intravenous studies, the elimination half-life of lidocaine was statistically signiﬁcantly longer in elderly patients (2.5 hours) than in younger patients (1.5 hours).

13 NONCLINICAL TOXICOLOGY

13.1 Carcinogenesis, Mutagenesis, Impairment of Fertility

Carcinogenesis

Long-term studies in animals have not been performed to evaluate the carcinogenic potential of lidocaine.

Mutagenesis

No mutagenic potential of lidocaine was demonstrated in the in vitro Ames Bacterial Reverse Mutation Assay, the in vitro chromosome aberration assay using Chinese hamster ovary cells, and the in vivo mouse micronucleus assay.

Impairment of Fertility

Zingo™ was not formally evaluated for effects on fertility. Significant systemic exposure to lidocaine is not expected under recommended conditions of use of Zingo™, as lidocaine levels were below the limit of detection in human studies. Lidocaine has been previously tested in animal studies for effects on fertility, however. The following ratios are based on the assumption that the applied dose is completely absorbed through the skin.

Lidocaine did not affect fertility in female rats when given via continuous subcutaneous infusion via osmotic minipumps up to doses of 250 mg/kg/day [1500 mg/m^2 or 5000-fold higher than the SDA of 0.5 mg lidocaine in a 60 kg individual (0.3 mg/m^2)]. Although lidocaine treatment of male rats increased the copulatory interval and led to a dose-related decreased homogenization resistant sperm head count, daily sperm production, and spermatogenic efficiency, the treatment did not affect overall fertility in male rats when given subcutaneous doses up to 60 mg/kg (360 mg/m^2 or 1200-fold the SDA).

14 CLINICAL STUDIES

Efficacy in Adults

The efficacy of Zingo™ in adults was evaluated in a randomized, double-blind, parallel-arm, sham-placebo controlled trial in which adult patients who required a venipuncture or peripheral venous cannulation received either Zingo™ or a sham placebo device.

Patients were treated with Zingo™ or a placebo device at the antecubital fossa or back of the hand, between one and three minutes prior to venipuncture or peripheral venous cannulation. Measurements of pain were made immediately following the procedure. Efficacy was measured using a continuous 100 mm visual analogue scale ranging from 0 (“no pain”) to 100 (“worst possible pain”).

Many of the patients had chronic medical problems such as depression, hypertension, hypothyroidism, and hyperlipidemia and over one fourth of the population may have been at higher than average risk of dermal bleeding due to use of concomitant medications such as NSAIDs, aspirin, and corticosteroids.

Treatment with active drug resulted in less pain compared with placebo (see Table 1).

Table 1: Visual Analogue Scale Score (Full Safety/Efﬁcacy Population)
 | Adult Study
 | Active (N = 345) | Placebo (N = 348)
Adjusted Mean, LSM^1 | 11.61 | 16.23
Difference in LSMs (SE^2) | -4.62 (1.55)
95% Confidence Limits | -7.67, -1.57

^1 least squares mean ^2 standard error

However, efficacy was primarily seen in patients undergoing venipuncture at the antecubital fossa, while patients undergoing cannulation at the back of the hand did not demonstrate a difference between active and sham administrations.

Efficacy in Pediatric Patients

The efficacy of Zingo™ in patients 3–18 years of age was evaluated in two randomized, double-blind, parallel-arm, sham-placebo controlled trials in which pediatric patients received either Zingo™ or a sham placebo device.

The overall patient population consisted of healthy pediatric patients as well as those with acute and chronic medical conditions (i.e., diabetes, asthma, seizure disorder, juvenile rheumatoid arthritis and renal or hepatic transplantation) ages 3–18 years. All patients required peripheral venipuncture or intravenous cannulation as part of their clinical care.

Two efficacy trials (Studies 1 and 2) were conducted during which patients were treated with Zingo™ or a placebo device at the back of hand or antecubital fossa, between one and three minutes prior to venipuncture or peripheral venous cannulation. Measurements of pain were made immediately following the venous procedure. Efficacy was measured using a modified version of the Wong-Baker FACES pain rating scale [a categorical 6-point scale containing 6 faces ranging from 0 (“no hurt”) to 5 (“hurts worst”)].

In both studies, treatment with active drug resulted in less pain, from venipuncture or peripheral IV cannulation, compared with placebo (See Table 2).

Table 2: Modiﬁed FACES Scale Score (ITT Population), Studies 1 and 2
 | Study 1 |  | Study 2
 | Active (N = 292) | Placebo (N = 287) | Active (N = 269) | Placebo (N = 266)
Adjusted Mean, LSM^1 | 1.77 | 2.10 | 1.38 | 1.77
Difference in LSMs (SE^2) | -0.33 (0.13) |  | -0.39 (0.13)
95% Confidence Limits | -0.58, -0.08 |  | -0.65, -0.13

^1 least squares mean ^2 standard error

16 HOW SUPPLIED/STORAGE AND HANDLING

NDC 61388-001-48 Zingo™ (lidocaine hydrochloride monohydrate) powder intradermal injection system contains 0.5 mg of sterile lidocaine hydrochloride monohydrate. Zingo™ is a single-use device packaged in an individual clear pouch. Twelve pouched devices are placed in labeled cartons.

Cartons are stored at controlled room temperature (15–30°C, 59–86°F).

17 PATIENT COUNSELING INFORMATION

Patients should be made aware that a sound similar to that of a popping balloon is emitted at the time Zingo™ is actuated.

Patients should be informed that skin reactions including erythema, petechiae, pruritus and edema may occur.
Manufactured by:
Powder Pharmaceuticals, Inc.
Hong Kong, China

Zingo™ is a trademark of Powder
Pharmaceuticals, Incorporated.

Distributed by:
[Medline Logo]
Medline Industries, Inc.,
Mundelein, IL 60060, USA (RA14)
REF: 53329-200-57
Under license by Marathon Pharmaceuticals, LLC.

Package/Label Display Panel

NDC 61388-001-48
Zingo ™
(lidocaine hydrochloride monohydrate)
powder intradermal injection system
0.5mg
RX only.
Manufactured by:
Powder Pharmaaceuticals, Inc.
Hong Kong, China